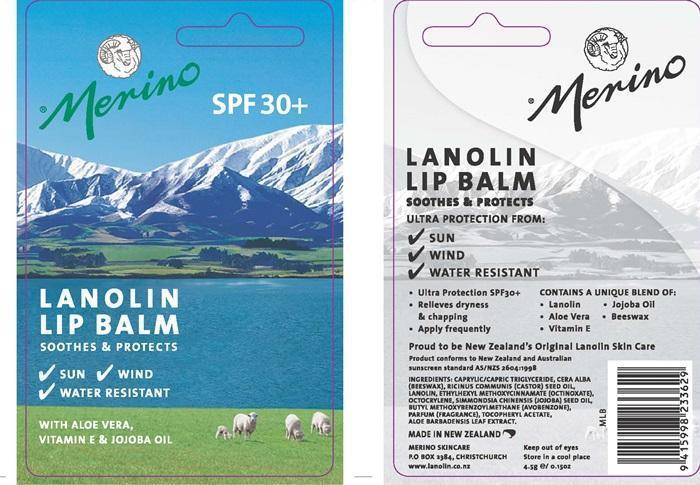 DRUG LABEL: Merino Lip SPF 30
NDC: 34834-001 | Form: LIPSTICK
Manufacturer: Merino Lanolin Skin Care Products
Category: otc | Type: HUMAN OTC DRUG LABEL
Date: 20141114

ACTIVE INGREDIENTS: OCTINOXATE 279 mg/4.5 g; OCTOCRYLENE 185 mg/4.5 g; AVOBENZONE 185 mg/4.5 g
INACTIVE INGREDIENTS: MEDIUM-CHAIN TRIGLYCERIDES; WHITE WAX; CASTOR OIL; LANOLIN; JOJOBA OIL; .ALPHA.-TOCOPHEROL ACETATE; ALOE VERA LEAF

Ingredients

ETHYLHEXYL METHOXYCINNAMATE (OCTINOXATE)
OCTOCRYLENE
BUTYL METHOXYBENZOYLMETHANE (AVOBENZONE)

Purpose

SOOTHES and PROTECTS

Keep out of reach of children

Enter section text here

Uses

- Ultra Protection SPF 30+
- Relieves dryness and chapping

Warning

Keep out of eyes

Directions

- Apply frequently

Ingredients

CAPRYLIC/CAPRIC TRIGLYCERIDE, CERA ALBA (BEESWAX), RICINUS COMMUNIS (CASTOR) SEED OIL, LANOLIN, SIMMONDSIA CHINENSIS (JOJOBA)SEED OIL, PARFUM (FRAGRANCE), TOCOPHERYL ACETATE, ALOE BARBADENSIS LEAF EXTRACT

Product Label

Merino

SPF 30+

LANOLIN LIP BALM
SOOTHES and PROTECTS
SUN
WIND
WATER RESISTANT

WITH ALOE VERA, VITAMIN E and JOJOBA OIL

CONTAINS A UNIQUE BLEND OF:
Lanolin
Aloe Vera
Vitamin E
Jojoba Oil
Beeswax

Proud to be New Zealand's Original Lanolin Skin Care

Product conforms to New Zealand and Australian sunscreen standard AS/NZS 2604:1998

MADE IN NEW ZEALAND
MERINO SKINCARE
P.O. Box 2384 CHRISTCHURCH

www.lanolin.co.nz

Store in a cool place

4.5 g e/ 0.15 oz